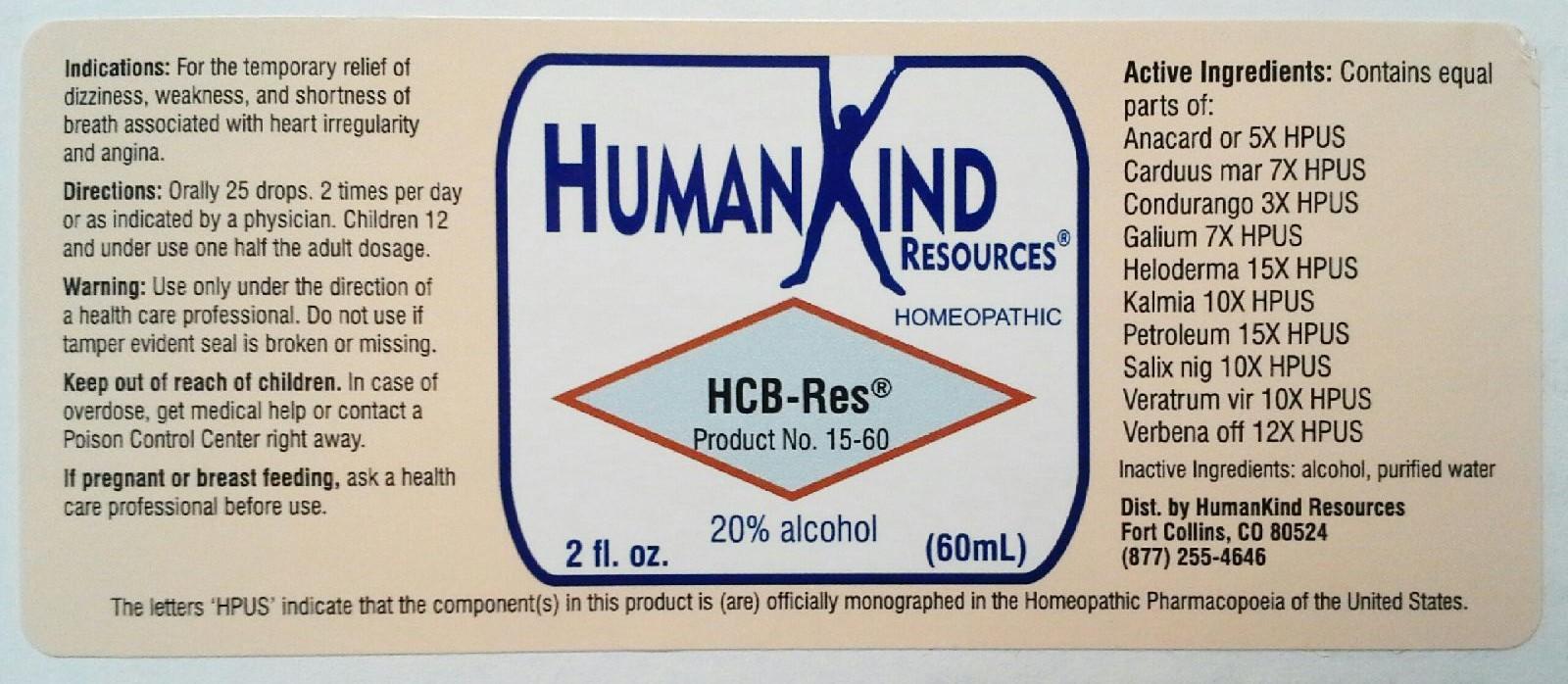 DRUG LABEL: HCB-Res
NDC: 64616-093 | Form: LIQUID
Manufacturer: Vitality Works, Inc.
Category: homeopathic | Type: HUMAN OTC DRUG LABEL
Date: 20251217

ACTIVE INGREDIENTS: SEMECARPUS ANACARDIUM JUICE 5 [hp_X]/1 mL; MILK THISTLE 7 [hp_X]/1 mL; MARSDENIA CONDURANGO BARK 3 [hp_X]/1 mL; GALIUM APARINE 7 [hp_X]/1 mL; HELODERMA HORRIDUM VENOM 15 [hp_X]/1 mL; KALMIA LATIFOLIA LEAF 10 [hp_X]/1 mL; KEROSENE 15 [hp_X]/1 mL; SALIX NIGRA BARK 10 [hp_X]/1 mL; VERATRUM VIRIDE ROOT 10 [hp_X]/1 mL; VERBENA OFFICINALIS 12 [hp_X]/1 mL
INACTIVE INGREDIENTS: ALCOHOL; WATER

HCB-Res

HCB-Res

Anacardium Orientale 5X Kalmia Latifolia 10X

Carduus Marianus 7X Petroleum 15X

Condurango 3X Salix Nigra 10X

Galium Aparine 7X Veratrum Viride 10X

Heloderma 15X Verbena Officinalis 12X

HCB-Res

Alcohol, Purified Water

HCB-Res

Use only under direction of a health care professional. Do not use if tamper evident seal is broken or missing.

HCB-Res

Keep out of reach of children. In case of overdose, get medical help or contact a Poison Control Center right away.

HCB-Res

For the temporary relief of dizziness, weakness, and shortness of breath associated with heart irregularity and angina.

HCB-Res

Orally 25 drops, 2 times per day or as indicated by a physcian. Children 12 and under use one half the adult dosage.

HCB-Res

Helps with circulatory system and blood.